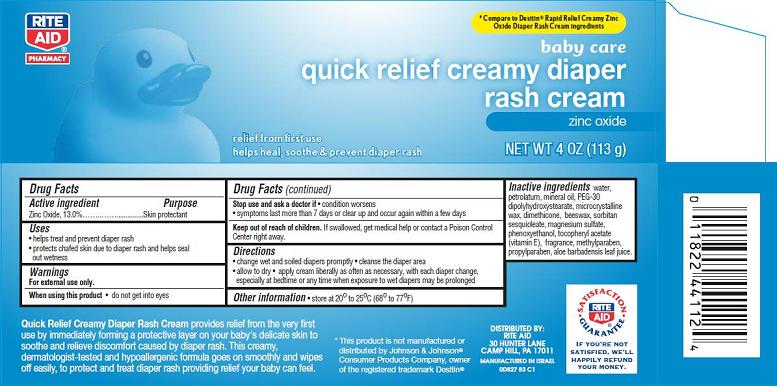 DRUG LABEL: Quick Relief Creamy Diaper Rash
NDC: 11822-8271 | Form: CREAM
Manufacturer: Rite Aid Corporation
Category: otc | Type: HUMAN OTC DRUG LABEL
Date: 20140307

ACTIVE INGREDIENTS: ZINC OXIDE 13 g/100 g
INACTIVE INGREDIENTS: WATER; PETROLATUM; MINERAL OIL; ROYAL JELLY; PEG-30 DIPOLYHYDROXYSTEARATE; MICROCRYSTALLINE WAX; POLYGLYCERYL-3 DIISOSTEARATE; DIMETHICONE; SORBITAN SESQUIOLEATE; MAGNESIUM SULFATE; PHENOXYETHANOL; .ALPHA.-TOCOPHEROL ACETATE; METHYLPARABEN; PROPYLPARABEN; ALOE VERA LEAF; POTASSIUM HYDROXIDE

Quick Relief Creamy Diaper Rash

Active ingredient

Zinc Oxide........13.0%

Purpose

Skin protectant

Uses

- helps treat and prevent diaper rash
- protects chafed skin due to diaper rash and helps seal out wetness

Warnings

For external use only.

When using this product

- do not get into eyes

Stop use and ask a doctor if

- condition worsens
- symptoms last more than 7 days or clear up and occur again within a few days

Keep Out of Reach of Children.

If swallowed, get medical help or contact a Poison Control Center right away.

Directions

- change wet and soiled diapers promptly
- cleanse the diaper area
- allow to dry
- apply cream liberally as often as necessary, with each diaper change, especially at bedtime or any time when exposure to wet diapers may be prolonged

Other Information

- store at 20° to 25°C (68° to 77°F)

Inactive ingredients

water, petrolatum, mineral oil, PEG-30 dipolyhydroxystearate, microcrystalline wax, dimethicone, beeswax, sorbitan sesquioleate, magnesium sulfate, phenoxyethanol, tocopheryl acetate (vitamin E), fragrance, methylparaben, propylparaben, aloe barbadensis leaf juice.

Package/Label Principal Display Panel

quick relief creamy diaper rash cream
zinc oxide

relief from first use
helps heal, soothe & prevent diaper rash

NET WT 4 OZ. (113 g)

*Compare to Desitin® Rapid Relief Creamy Zinc Oxide Diaper Rash Cream ingredients

Quick Relief Creamy Diaper Rash Cream provides relief from the very first use by immediately forming a protective layer on your baby’s delicate skin to soothe and relieve discomfort caused by diaper rash. This creamy, dermatologist-tested and hypoallergenic formula goes on smoothly and wipes off easily, to protect and treat diaper rash providing relief your baby can feel.

*This product is not manufactured or distributed by Johnson & Johnson®
Consumer Products Company, owner of the registered trademark Desitin®

DISTRIBUTED BY:
RITE AID,
30 HUNTER LANE
CAMP HILL, PA 17011

MADE IN ISRAEL

0D827 B3 C1

SATISFACTION GUARANTEE

IF YOU’RE NOT SATISFIED, WE’LL HAPPILY REFUND YOUR MONEY.

Carton Label